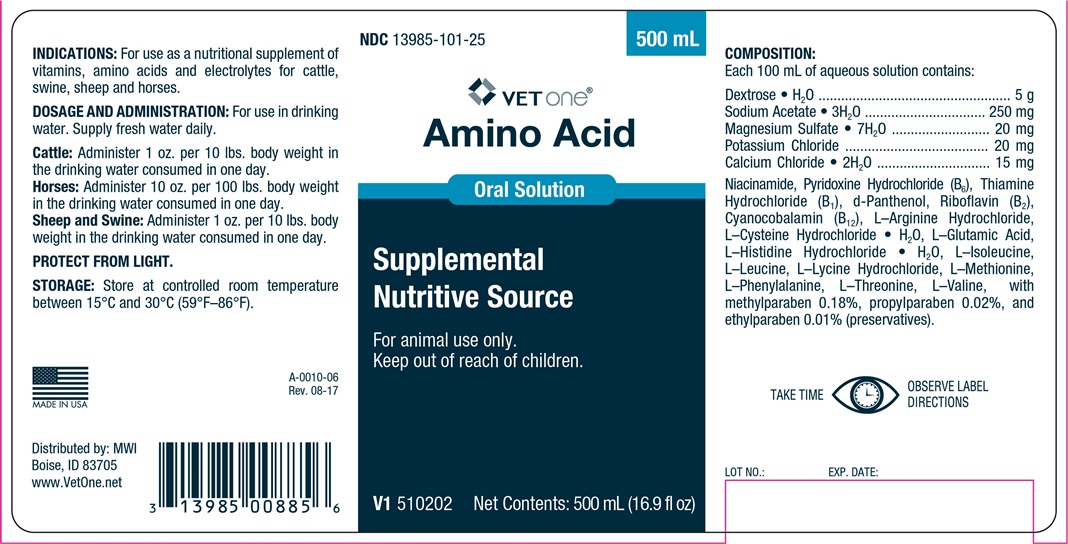 DRUG LABEL: AMINO ACID 
NDC: 13985-101 | Form: SOLUTION
Manufacturer: MWI/VetOne
Category: animal | Type: OTC ANIMAL DRUG LABEL
Date: 20180117

ACTIVE INGREDIENTS: DEXTROSE MONOHYDRATE 5000 mg/100 mL; CALCIUM CHLORIDE ANHYDROUS 15 mg/100 mL; MAGNESIUM SULFATE HEPTAHYDRATE 20  mg/100 mL; POTASSIUM CHLORIDE 20 mg/100 mL; SODIUM ACETATE ANHYDROUS 250 mg/100 mL
INACTIVE INGREDIENTS: VALINE

AMINO ACID ORAL SOLUTION

INDICATIONS AND USAGE

Supplemental Nutritive Source

For animal use only.

Keep out of reach of children.

INDICATIONS

For use as a nutritional supplement of vitamins, amino acids and electrolytes for cattle, swine, sheep and horses.

DOSAGE AND ADMINISTRATION

For use in drinking water. Supply fresh water daily.

Cattle: Administer 1 oz. per 10 pounds body weight in the drinking water consumed in one day.

Horses: Administer 10 ozs. per 100 pounds body weight in the drinking water consumed in one day.

Sheep and Swine: Administer 1 oz. per 10 pounds body weight i the drinking water consume in one day.

STORAGE AND HANDLING

PROTECT FROM LIGHT.

Store in controlled room temperature between 15o and 30oC (59o-86oF).

TAKE TIME OBSERVE LABEL DIRECTIONS

COMPOSITION

Each 100 mL of aqueous solution contains:

Dextrose•H2O ....................................... 5 g

Sodium Acetate•3H2O ..................... 250 mg

Magnesium Sulfate•7H2O .................. 20 mg

Potassium Chloride ........................... 20 mg

Calcium Chloride•2H2O ..................... 15 mg

Comprised of: Niacinamide, Pyridoxine HCl (B6), d-Panthenol, Riboflavin (B2), Cyanocobalamin (B12), L-Argenine HCl, L-Cysteine HCl H2O, L-Glutamic Acid, L-Histidine HCl H2O, L-Isoleucie, L-Leucine, L-Lycine HCl, L-Methionine, L-Phenylalamine, L-Theonine, L-Valine with Methylparaben 0.18%, Ethylparaben 0.01%, Propylparaben 0.02%.